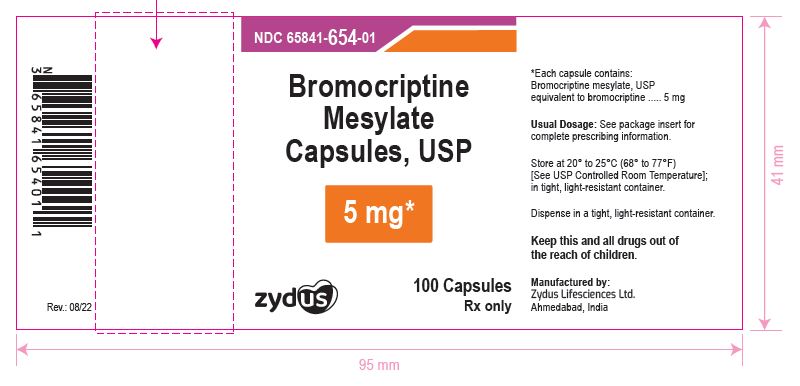 DRUG LABEL: Bromocriptine mesylate
NDC: 65841-654 | Form: CAPSULE
Manufacturer: Zydus Lifesciences Limited
Category: prescription | Type: HUMAN PRESCRIPTION DRUG LABEL
Date: 20241125

ACTIVE INGREDIENTS: BROMOCRIPTINE MESYLATE 5 mg/1 1
INACTIVE INGREDIENTS: ALCOHOL; AMMONIA; BUTYL ALCOHOL; CARRAGEENAN; FERRIC OXIDE RED; FERROSOFERRIC OXIDE; HYPROMELLOSE 2910 (15 MPA.S); ISOPROPYL ALCOHOL; LACTOSE MONOHYDRATE; MAGNESIUM STEARATE; MALEIC ACID; POTASSIUM HYDROXIDE; PROPYLENE GLYCOL; SHELLAC; SILICON DIOXIDE; TITANIUM DIOXIDE; WATER

Bromocriptine Mesylate Capsules, USP

PACKAGE LABEL.PRINCIPAL DISPLAY PANEL

NDC 65841-654-01 in bottle of 100 Capsules

Bromocriptine Mesylate Capsules USP, 5 mg

Rx only

100 Capsules